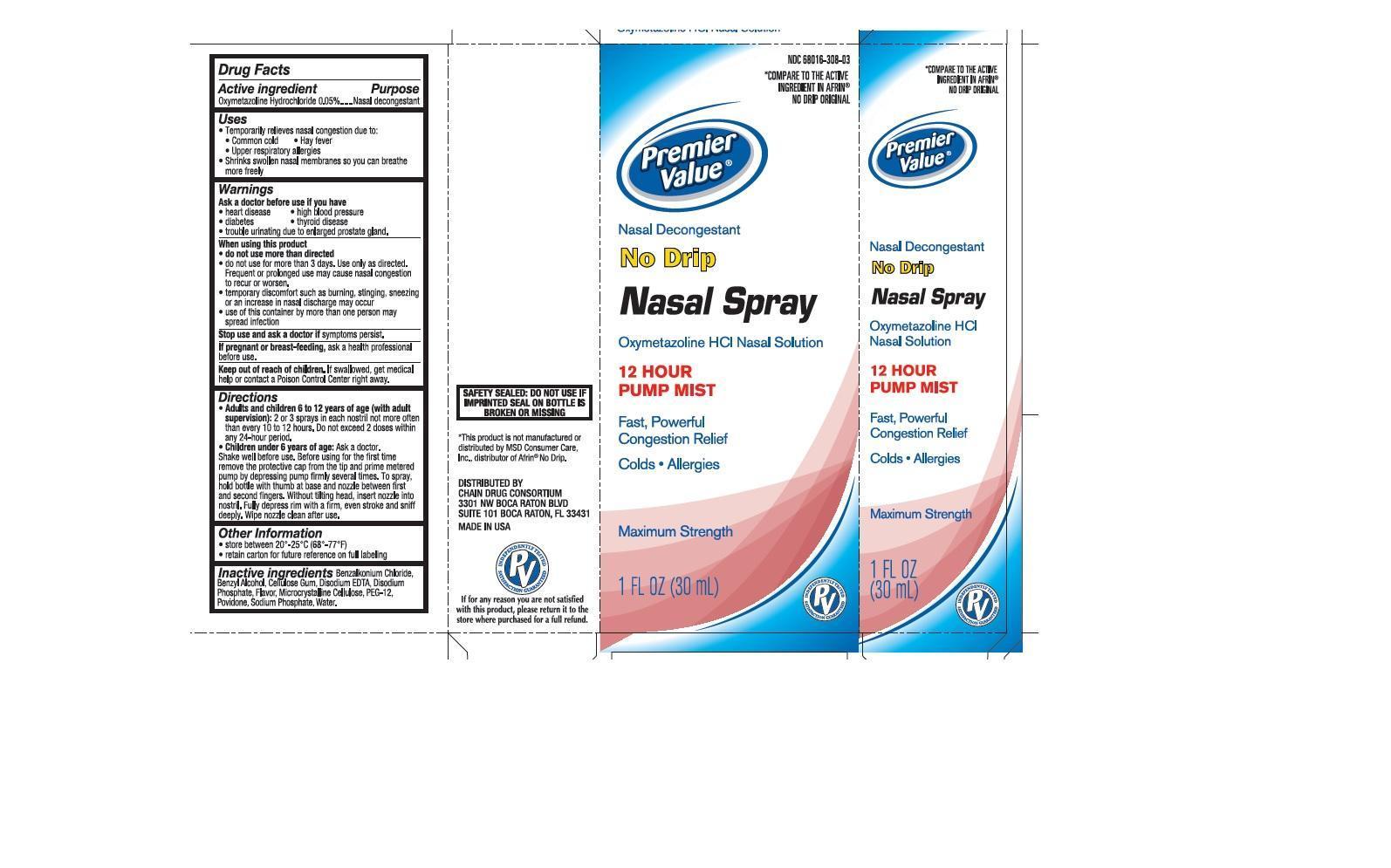 DRUG LABEL: No Drip
NDC: 68016-308 | Form: SPRAY
Manufacturer: Chain Drug Consortium
Category: otc | Type: HUMAN OTC DRUG LABEL
Date: 20151014

ACTIVE INGREDIENTS: OXYMETAZOLINE HYDROCHLORIDE 0.05 mg/1 mL
INACTIVE INGREDIENTS: BENZALKONIUM CHLORIDE; BENZYL ALCOHOL; CARBOXYMETHYLCELLULOSE SODIUM; EDETATE DISODIUM; SODIUM PHOSPHATE, DIBASIC, ANHYDROUS; CELLULOSE, MICROCRYSTALLINE; POLYETHYLENE GLYCOL 600; POVIDONE; SODIUM PHOSPHATE; WATER

Nasal Spray

Active Ingredient

Oxymetazoline hydrochloride 0.05%

Purpose

Nasal Decongestant

Uses

- Temporarily relieves nasal congestion due to:
  - Common cold
  - Hay fever
  - Upper respiratory allergies
- Shrinks swollen nasal membranes so you can breathe more freely

Ask a doctor before use if you have

- heart disease
- high blood pressure
- diabetes
- thyroid disease
- trouble urinating due to an enlarged prostate gland.

When using this product

- do not use more than directed
- do not use for more than 3 days. Use only as directed. Frequent or prolonged use may cause nasal congestion to recur or worsen.
- temporary discomfort such as burning, stinging, sneezing, or an increase in nasal discharge may occur
- use of this container by more than one person may spread infection

Stop use and ask a doctor if

symptoms persist.

If pregnant or breast-feeding,

ask a health professional before use.

Keep out of reach of children.

If swallowed, get medical help or contact a Poison Control Center right away.

Directions

- Adults and children 6 to 12 years of age (with adult supervision): 2 or 3 sprays in each nostril not more often than every 10 to 12 hours. Do not exceed 2 doses within any 24-hour period.
- Children under 6 years of age: Ask a doctor.

Shake well before use. Before using for the first time remove the protective cap from the tip and prime metered pump by depressing pump firmly several times. To spray, hold bottle with thumb at base and nozzle between first and second fingers. Without tilting head, insert nozzle into nostril. Fully depress rim with a firm, even stroke and sniff deeply. Wipe nozzle clean after each use.

Other Information

- store between 20°-25°C (68°-77°F)
- retain carton for future reference on full labeling

Inactive Ingredients

Benzalkonium Chloride, Benzyl Alcohol, Cellulose Gum, Disodium EDTA, Disodium Phosphate, Flavor, Microcrystalline Cellulose, PEG-12, Povidone, Sodium Phosphate, Water.

Additional information listed on other panels

SAFETY SEALED: DO NOT USE IF IMPRINTED SEAL ON BOTTLE IS BROKEN OR MISSING.

*This product is not manufactured or distributed by MSD Consumer Care, INC., distributor of Afrin No Drip.

Distributed By:

Chain Drug Consortium

3301 NW Boca Raton Blvd, Suite 101

Boca Raton, FL 33431

Made in USA

If for any reason you are not satisfied with this product, please return it to the store where purchased for a full refund.

Principal Display

*Compare to the active ingredient in Afrin No Drip Original

Premier Value

Nasal Decongestant

No Drip

Nasal Spray

Oxymetazoline HCl Nasal Solution

12 HOUR PUMP MIST

Fast, Powerful Congestion Relief

- Colds
- Allergies

Maximum Strength

1 FL OZ (30 mL)